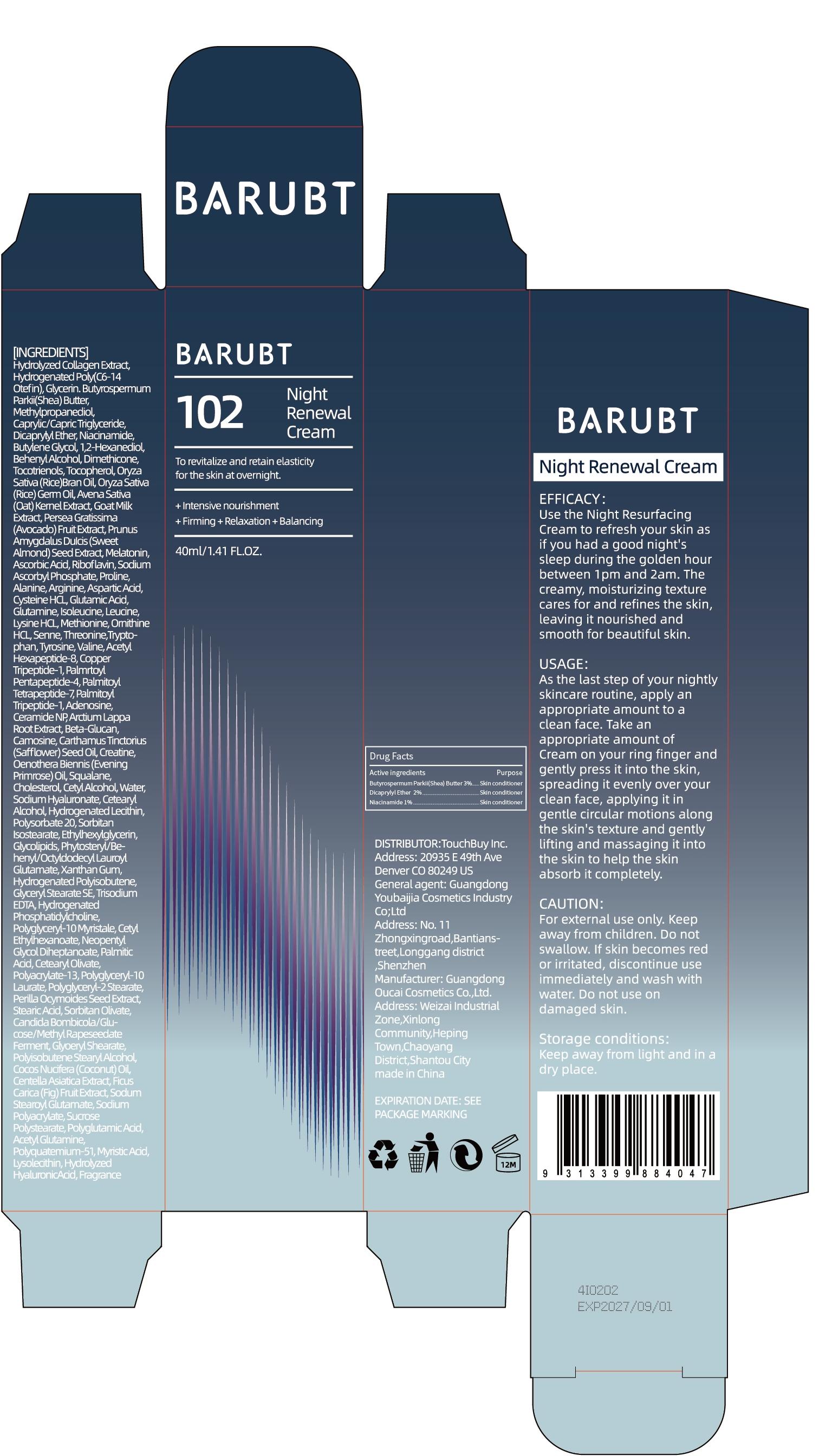 DRUG LABEL: BARUBT Night Renewal Cream
NDC: 84712-006 | Form: CREAM
Manufacturer: Guangdong Youbaijia Cosmetic Industry Co., Ltd
Category: otc | Type: HUMAN OTC DRUG LABEL
Date: 20240913

ACTIVE INGREDIENTS: BUTYROSPERMUM PARKII (SHEA) BUTTER UNSAPONIFIABLES 1.2 g/40 g; DICAPRYLYL ETHER 0.8 g/40 g; NIACINAMIDE 0.4 g/40 g
INACTIVE INGREDIENTS: METHYLPROPANEDIOL 1.2 g/40 g; BUTYLENE GLYCOL 0.4 g/40 g

ACTIVE INGREDIENT

Butyrospermum Parkii(Shea) Butter 3%
Dicaprylyl Ether 2%
Niacinamide 1%

INACTIVE INGREDIENT

Hydrolyzed Collagen Extract
Hydrogenated Poly(C6-14 Otefin)
Glycerin
Methylpropanediol
Caprylic/Capric Triglyceride
Butylene Glycol
1,2-Hexanediol
Behenyl Alcohol
Dimethicone
Tocotrienols
Tocopherol
Oryza Sativa (Rice)Bran Oil
Oryza Sativa (Rice) Germ Oil
Avena Sativa (Oat) Kernel Extract
Goat Milk Extract
Persea Gratissima (Avocado) Fruit Extract
Prunus Amygdalus DuIcis (Sweet Almond) Seed Extract
Melatonin
Ascorbic Acid
Riboflavin
Sodium Ascorbyl Phosphate
Proline
Alanine
Arginine
Aspartic Acid
Cysteine HCL
Glutamic Acid
Glutamine
Isoleucine
Leucine
Lysine HCL
Methionine
Ornithine HCL
Senne
Threonine
Tryptophan
Tyrosine
Valine
Acetyl Hexapeptide-8
Copper Tripeptide-1
Palmrtoyl Pentapeptide-4
Palmitoyl Tetrapeptide-7
Palmitoyl Tripeptide-1
Adenosine
Ceramide NP
Arctium Lappa Root Extract
Beta-Glucan
Camosine
Carthamus Tinctorius (Safflower) Seed Oil
Creatine
Oenothera Biennis (Evening Primrose) Oil
Squalane
Cholesterol
Cetyl Alcohol
Water
Sodium Hyaluronate
Cetearyl Alcohol
Hydrogenated Lecithin
Polysorbate 20
Sorbitan Isostearate
Ethylhexylglycerin
Glycolipids
Phytosteryl/Behenyl/Octyldodecyl Lauroyl Glutamate
Xanthan Gum
Hydrogenated Polyisobutene
Glyceryl Stearate SE
Trisodium EDTA
Hydrogenated Phosphatidylcholine
Polyglyceryl-10 Myristale
Cetyl Ethylhexanoate
Neopentyl Glycol Diheptanoate
Palmitic Acid
Cetearyl Olivate
Polyacrylate-13
Polyglyceryl-10 Laurate
Polyglyceryl-2 Stearate
Perilla Ocymoides Seed Extract
Stearic Acid
Sorbitan Olivate
Candida Bombicola/Glucose/Methyl Rapeseedate Ferment
Glyoeryl Shearate
Polyisobutene Stearyl Alcohol
Cocos Nucifera (Coconut) Oil
Centella Asiatica Extract
Ficus Carica (Fig) Fruit Extract
Sodum Stearoyl Glutamate
Sodium Polyacrylate
Sucrose Polystearate
Polyglutamic Acid
Acetyl Glutamine
Polyquatemium-51
Myristic Acid
Lysolecithin
Hydrolyzed HyaluronicAcid
Fragrance

Do not use on damaged skin.

Keep away from children. Do not swallow.

PURPOSE

Use the Night Resurfacing Cream to refresh your skin

QUESTIONS

Contact name: Jessie Peng
Company phone number: +1 818 579 7288
Company e-mail: jessie@registeragentllc.com

STOP USE

lf skin becomes red or irritated, discontinue use immediately and wash with water.

WHEN USING

keep out of eyes. Rinse with water to remove.

INDICATIONS AND USAGE

Use the Night Resurfacing Cream to refresh your skin as if you had a good night's sleep during the golden hour between 1pm and 2am.The
creamy, moisturizing texture cares for and refines the skin,leaving it nourished and smooth for beautiful skin.

WARNINGS

For external use only.

DOSAGE AND ADMINISTRATION

USAGE:

As the last step of your nightly skincare routine, apply an appropriate amount to a clean face. Take an appropriate amount of Cream on your ring finger and gently press it into the skin,spreading it evenly over your clean face, applying it ingentle circular motions along the skin's texture and gently lifting and massaging it into the skin to help the skin absorb it completely.

STORAGE AND HANDLING

Keep away from light and in adry place.